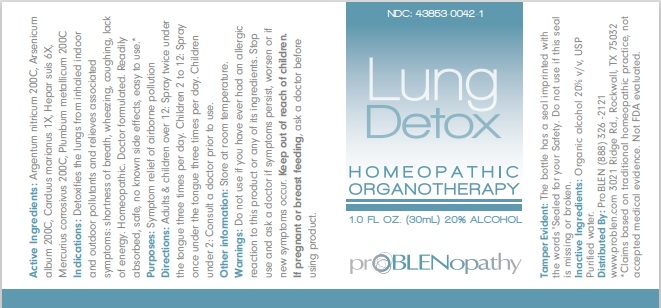 DRUG LABEL: Lung Detox
NDC: 43853-0042 | Form: LIQUID
Manufacturer: ProBLEN
Category: homeopathic | Type: HUMAN OTC DRUG LABEL
Date: 20221130

ACTIVE INGREDIENTS: SILVER NITRATE 200 [hp_C]/30 mL; ARSENIC TRIOXIDE 200 [hp_C]/30 mL; MILK THISTLE 1 [hp_X]/30 mL; PORK LIVER 6 [hp_X]/30 mL; MERCURIC CHLORIDE 200 [hp_C]/30 mL; LEAD 200 [hp_C]/30 mL
INACTIVE INGREDIENTS: WATER; ALCOHOL

Lung Detox

ACTIVE INGREDIENT

Active Ingredients: Argentum nitricum 200C, Arsenicum album 200C, Carduus marianus 1X, Hepar suis 6X, Mercurius corrosivus 200C,

Plumbum metallicum 200C.

*Claims based on traditional homeopathic practice, not accepted medical evidence. Not FDA evaluated.

INDICATIONS AND USAGE

Indications: Detoxifies the lungs from inhaled indoor and outdoor pollutants and relieves associated symptoms: shortness of breath, wheezing, coughing, lack of energy. Homeopathic. Doctor formulated. Readily absorbed, safe, no known side effects, easy to use.*

WARNINGS

Warnings: Do not use if you have ever had an allergic reaction to this product or any of its ingredients. Stop use and ask a doctor if symptoms persist, worsen or if new symptoms occur.

Keep out of reach of children. If pregnant or breast feeding, ask a doctor before using product.

DOSAGE AND ADMINISTRATION

Directions: Adults & children over 12: Spray twice under the tongue three times per day. Children 2 to 12: Spray once under the tongue three times per day. Children under 2: Consult a doctor prior to use.

Other information: Store at room temperature.

Tamper Evident: The bottle has a seal imprinted with the words "Sealed for your Safety". Do not use if this seal is missing or broken.

INACTIVE INGREDIENT

Inactive Ingredients: Organic alcohol 20% v/v, USP Purified water.

QUESTIONS

Distributed By: ProBLEN (888) 326 - 2121

www.problen.com 3021 Ridge Rd., Rockwall, TX 75032

PACKAGE LABEL

NDC: 43853-0042-1

Lung Detox

HOMEOPATHY

ORGANOTHERAPY

1.0 FL OZ. (30mL) 20% ALCOHOL

PURPOSE

Purposes: Symptom relief of airborne pollution